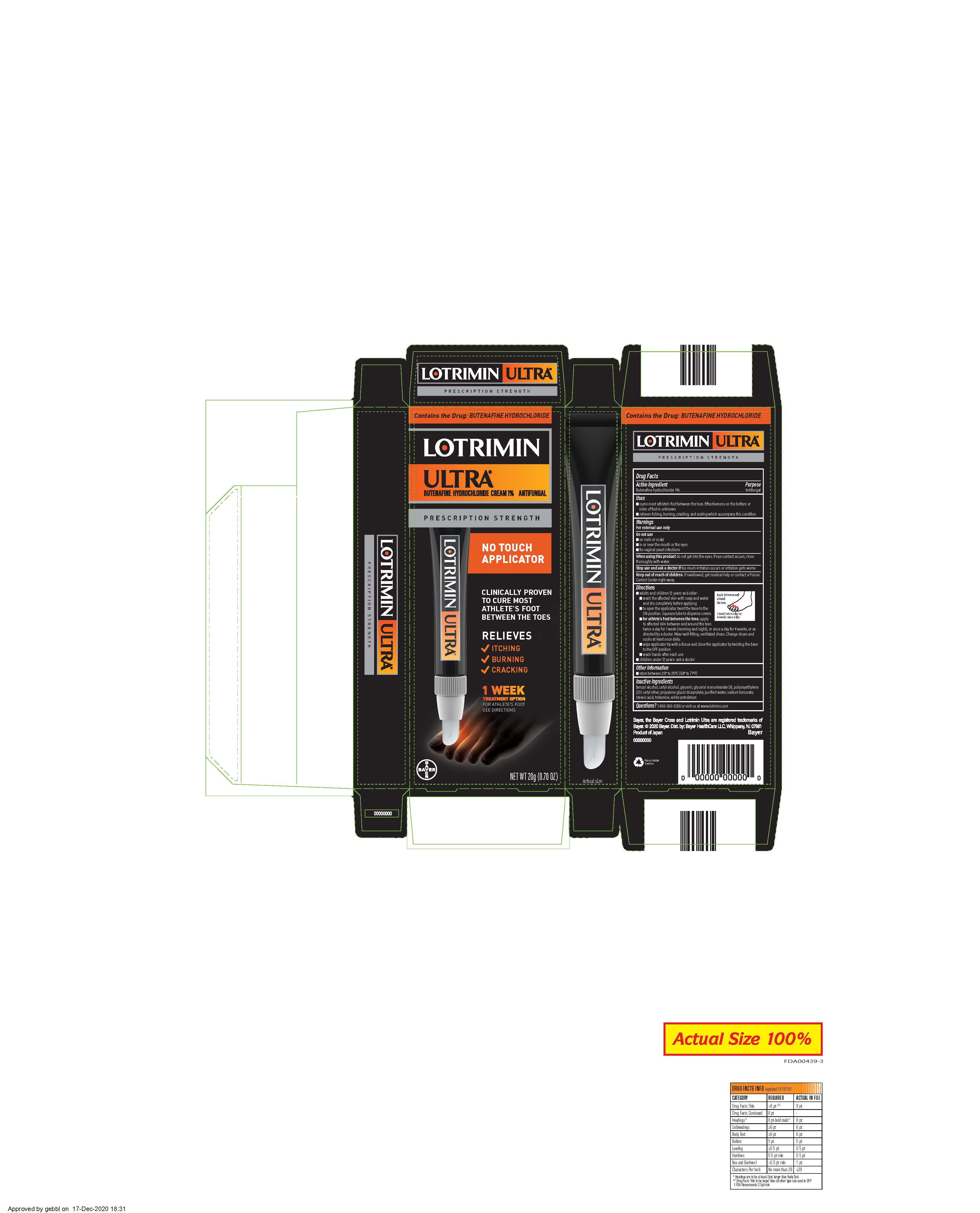 DRUG LABEL: Lotrimin Ultra
NDC: 11523-0082 | Form: CREAM
Manufacturer: Bayer Healthcare LLC.
Category: otc | Type: HUMAN OTC DRUG LABEL
Date: 20251204

ACTIVE INGREDIENTS: BUTENAFINE HYDROCHLORIDE 1 g/100 g
INACTIVE INGREDIENTS: STEARIC ACID; TROLAMINE; GLYCERIN; WHITE PETROLATUM; BENZYL ALCOHOL; CETYL ALCOHOL; WATER; SODIUM BENZOATE; CETETH-23; GLYCERYL MONOSTEARATE; PROPYLENE GLYCOL DICAPRYLATE

Lotrimin Ultra ®

Drug Facts

Active Ingredient

Butenafine hydrochloride 1%

Purpose

Antifungal

Uses

- cures most athlete's foot between the toes. Effectiveness on the bottom or sides of foot is unknown.
- relieves itching, burning, cracking, and scaling which accompany this condition

Warnings

For external use only

DO NOT USE

- on nails or scalp
- in or near the mouth or the eyes
- for vaginal yeast infections

When using this product do not get into the eyes. If eye contact occurs, rinse thoroughly with water.

Stop use and ask a doctor if too much irritation occurs or irritation gets worse

Keep out of reach of children. If swallowed, get medical help or contact a Poison Control Center right away.

Directions

- adults and children 12 years and older:
  - wash the affected skin with soap and water and dry completely before applying
  - to open the applicator, twist the base to the ON position. Squeeze tube to dispense cream.
  - for athlete's foot between the toes: apply to affected skin between and around the toes twice a day for 1 week (morning and night), or once a day for 4 weeks, or as directed by a doctor. Wear well-fitting, ventilated shoes. Change shoes and socks at least once daily.
  - wipe applicator tip with a tissue and close the applicator by twisting the base to the OFF position
  - wash hands after each use
- children under 12 years: ask a doctor

Other information

- store between 20° to 25°C (68° to 77°F)

Inactive ingredients

benzyl alcohol, cetyl alcohol, glycerin, glyceryl monostearate SE, polyoxyethylene (23) cetyl ether, propylene glycol dicaprylate, purified water, sodium benzoate, stearic acid, trolamine, white petrolatum

Questions?

1-866-360-3266 or visit us at www.lotrimin.com

PACKAGE LABEL

LOTRIMIN ULTRA ®

BUTENAFINE HYDROCHLORIDE CREAM 1% ANTIFUNGAL
NET WT 20g (0.70 OZ)